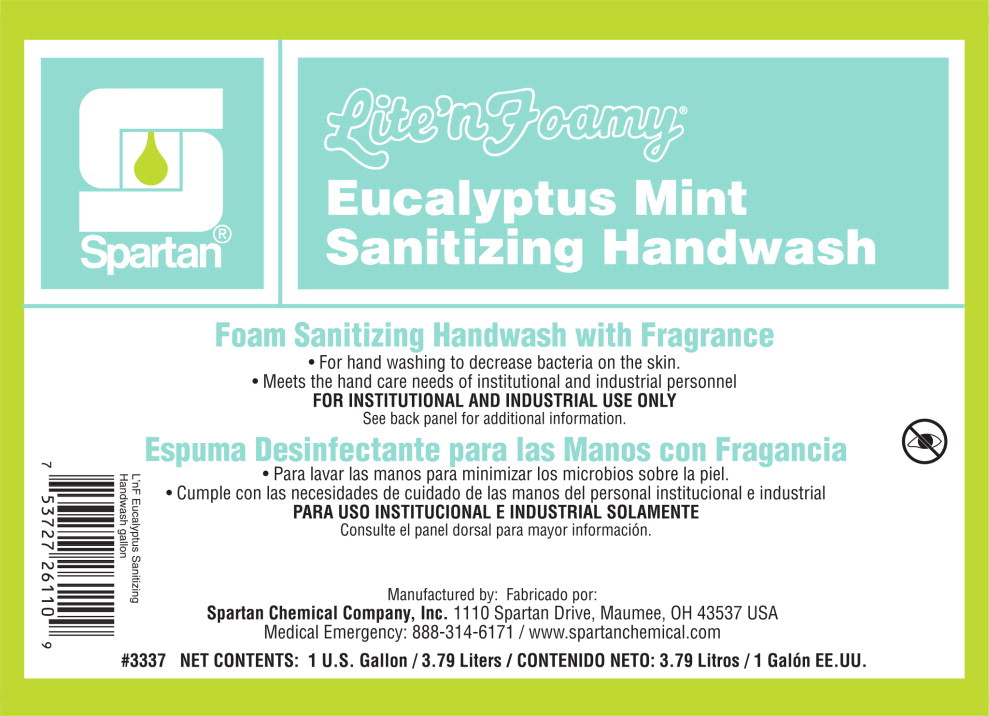 DRUG LABEL: Lite nFoamy Eucalyptus Mint Sanitizing Handwash
NDC: 64009-332 | Form: SOAP
Manufacturer: Spartan Chemical Company, Inc.
Category: otc | Type: HUMAN OTC DRUG LABEL
Date: 20251007

ACTIVE INGREDIENTS: BENZALKONIUM CHLORIDE 1.3 g/1 L
INACTIVE INGREDIENTS: WATER; COCO GLUCOSIDE; LAURTRIMONIUM CHLORIDE; CITRIC ACID MONOHYDRATE; MYRISTAMIDOPROPYLAMINE OXIDE; LAURAMIDOPROPYLAMINE OXIDE; CAPRYLYL/CAPRYL GLUCOSIDE

Drug Facts

Active Ingredients

Benzalkonium Chloride 0.13%

Purpose

Antimicrobial

Uses

- For hand washing to decrease bacteria on the skin.
- Recommended for repeated use.

Warnings

- For external use only

When using this product avoid contact with eyes. In case of eye contact, flush eyes with water.

Stop use and ask a doctor if irritation and redness develops, or if condition persists for more than 72 hours.

Keep out of reach of children.

If swallowed, get medical help or contact a Poison Control Center right away.

Directions

- Pump a small amount of foam into palm of hand.
- Rub thoroughly over all surfaces of both hands for 15 seconds.
- Rinse with potable water.

Inactive Ingredients

Water, Coco-Glucoside, Laurtrimonium Chloride, Cocamidopropylamine Oxide, Citric Acid, Fragrance

Questions?

1-800-537-8990

Principal Display Panel - Container Label

Spartan®

Lite'nFoamy®

Eucalyptus Mint
Sanitizing Handwash

Foam Sanitizing Handwash with Fragrance

- For hand washing to decrease bacteria on the skin
- Meets the hand care needs of institutional and industrial personnel

FOR INSTITUTIONAL AND INDUSTRIAL USE ONLY

See back panel for additional information.

Manufactured by
Spartan Chemical Company, Inc. 1110 Spartan Drive, Maumee, OH 43537 USA

Medical Emergency: 888-314-6171 / www.spartanchemical.com

Net Contents: 1 U.S. Gallon / 3.79 Liters